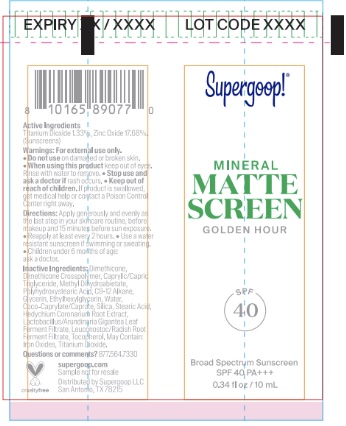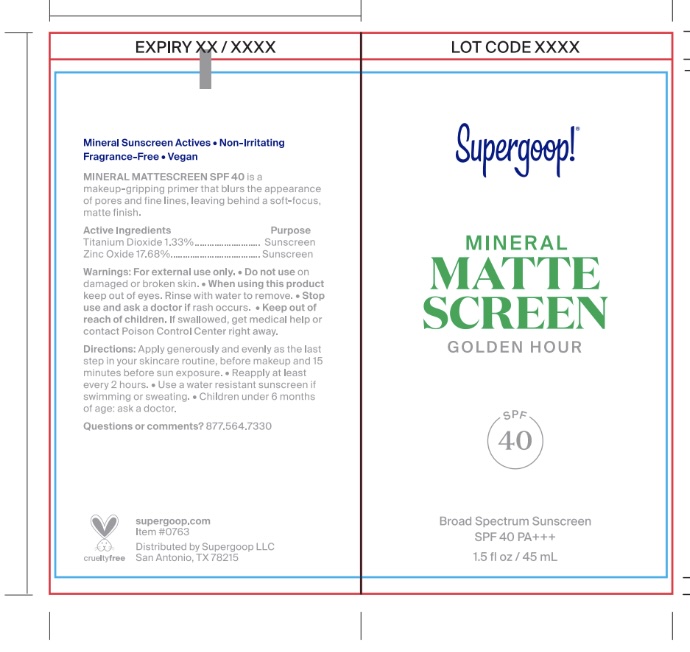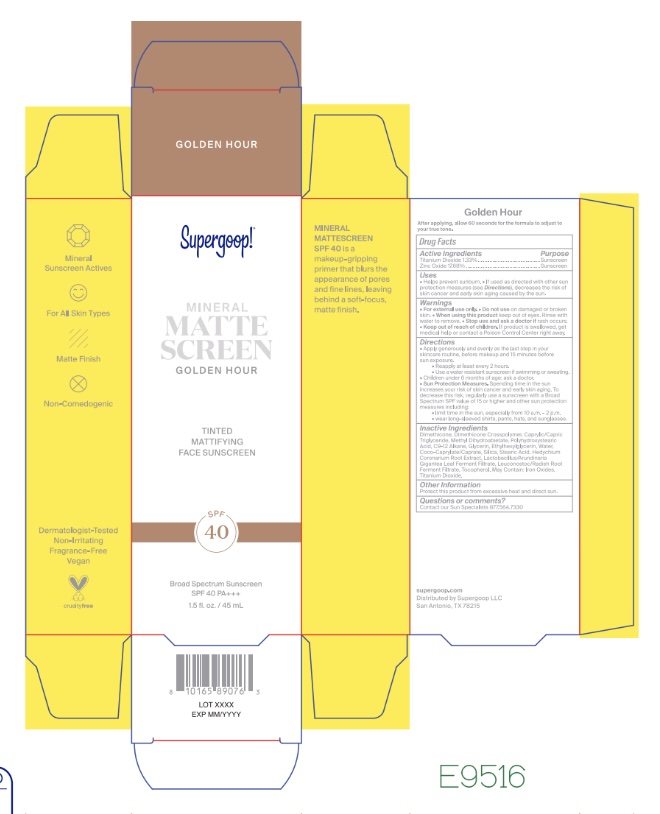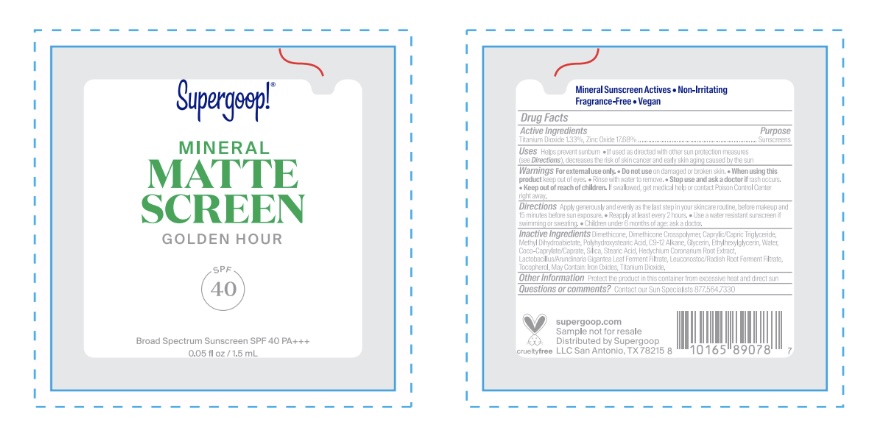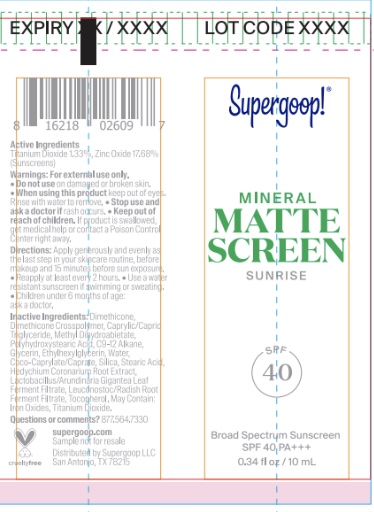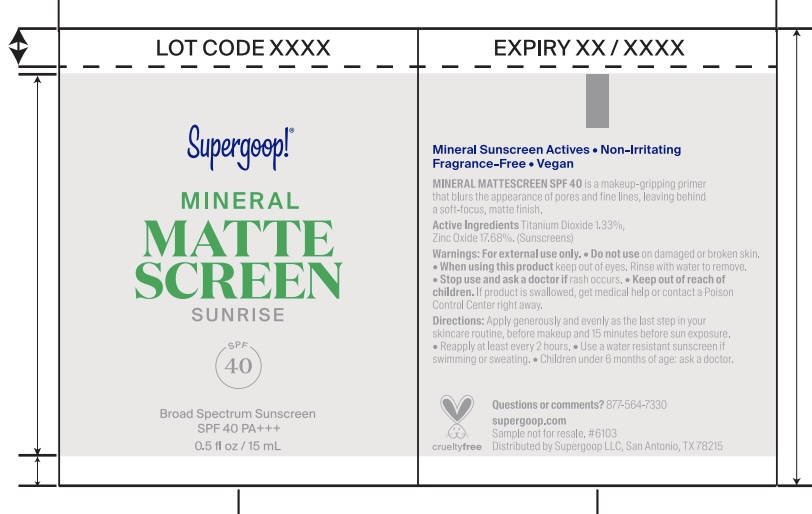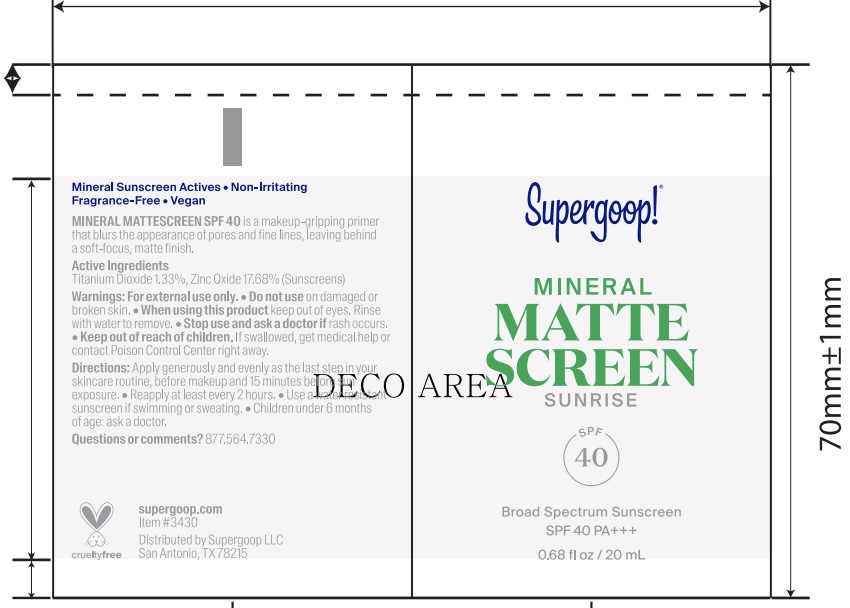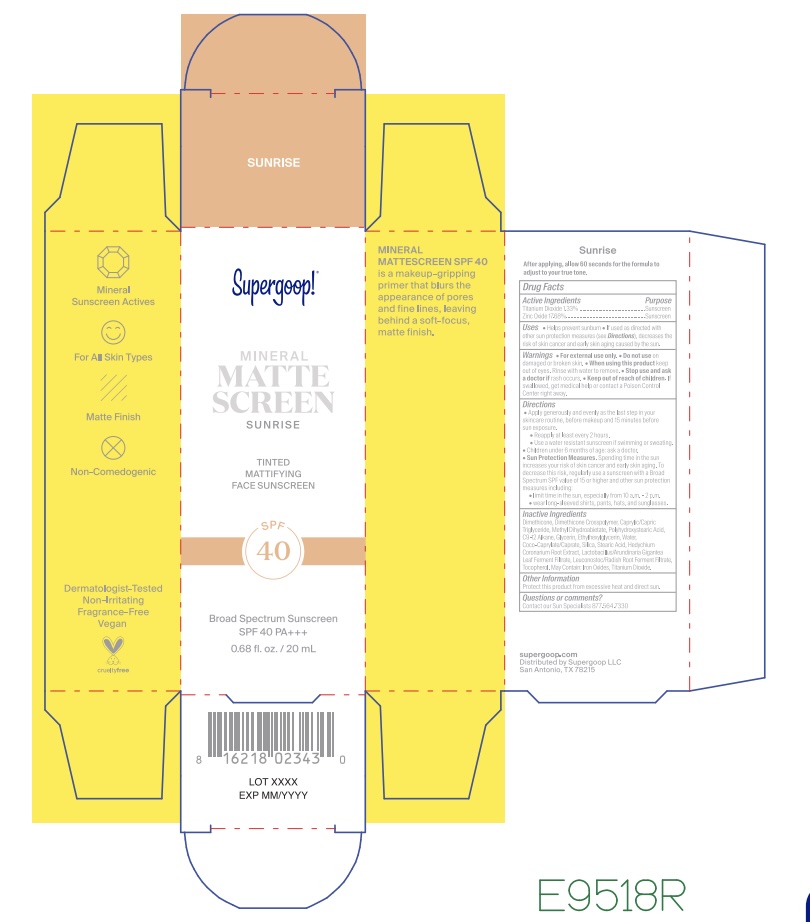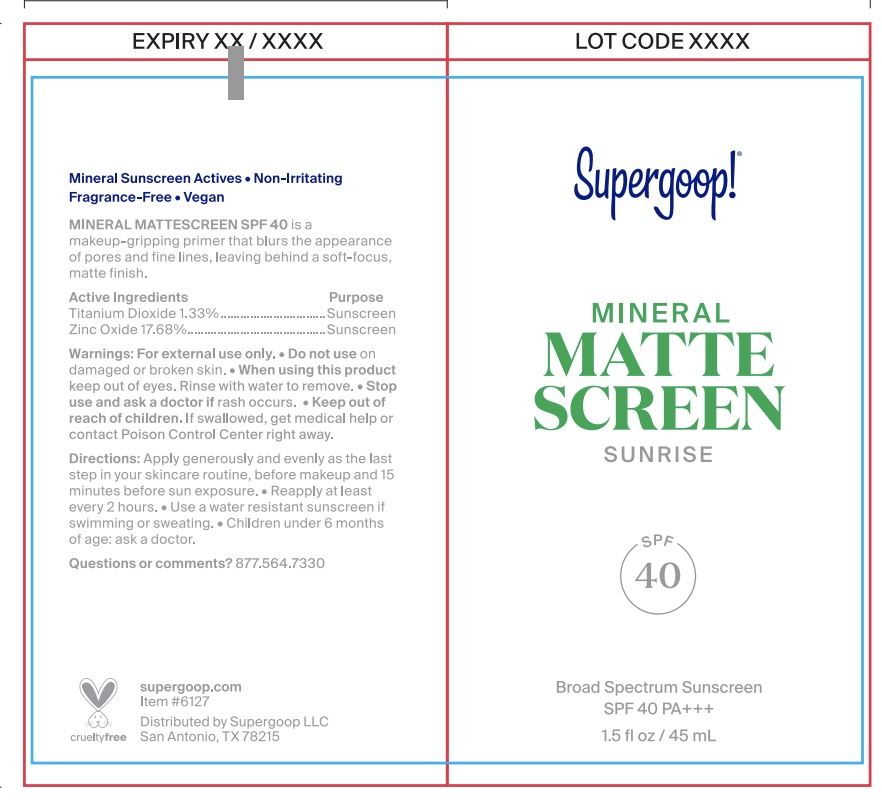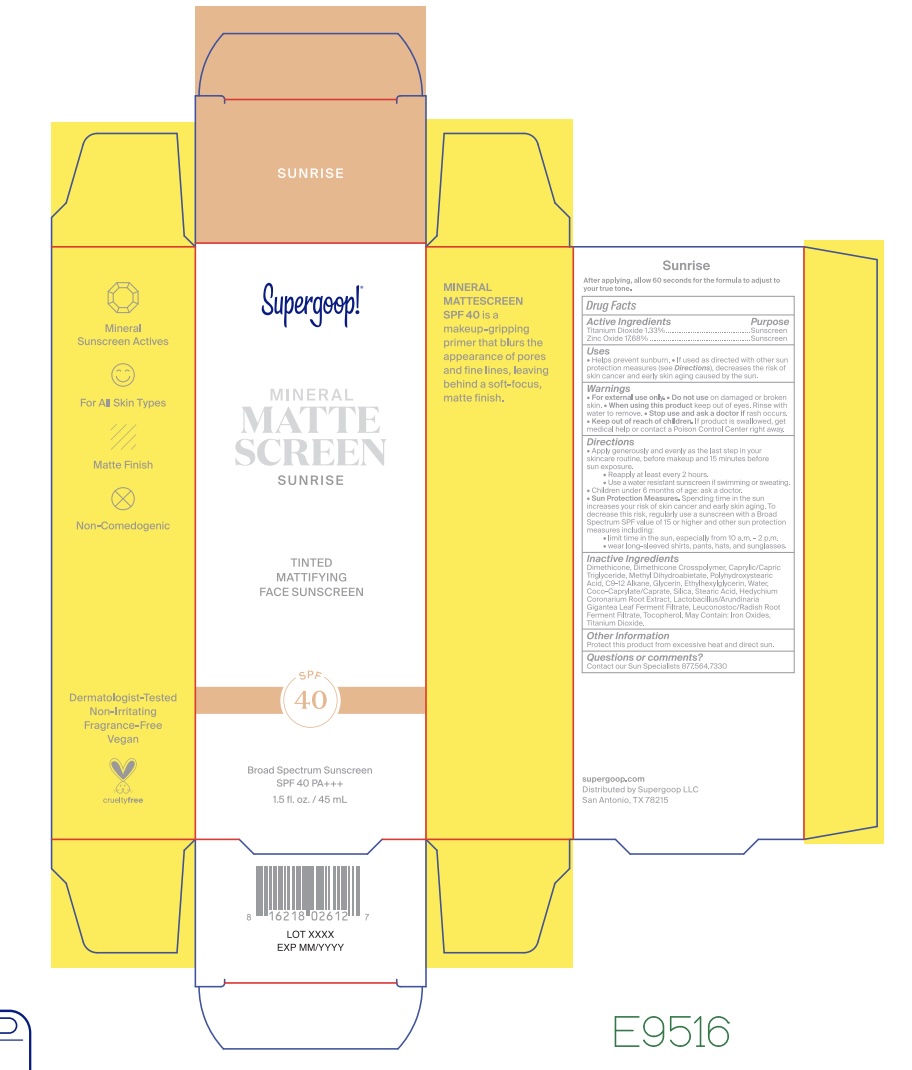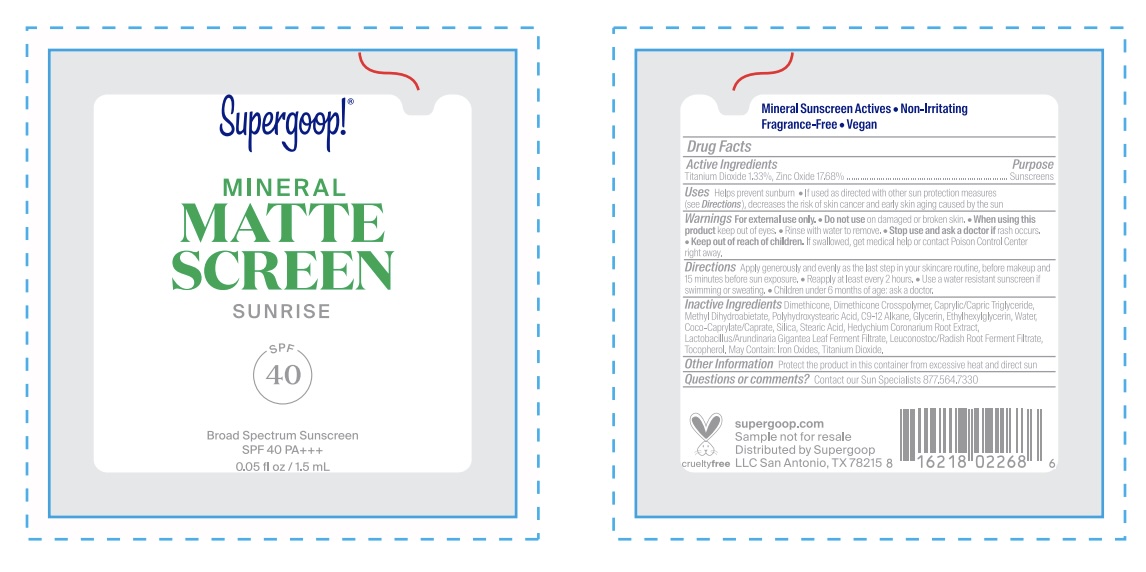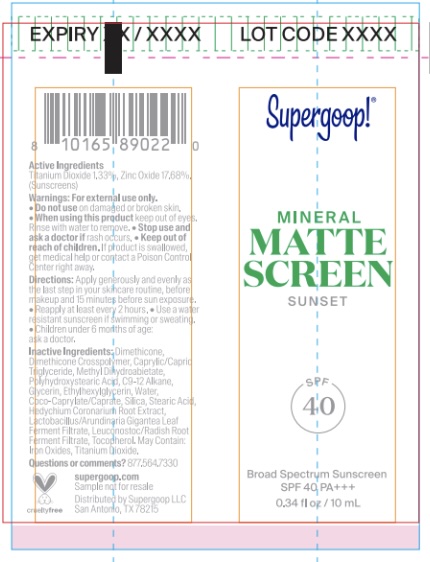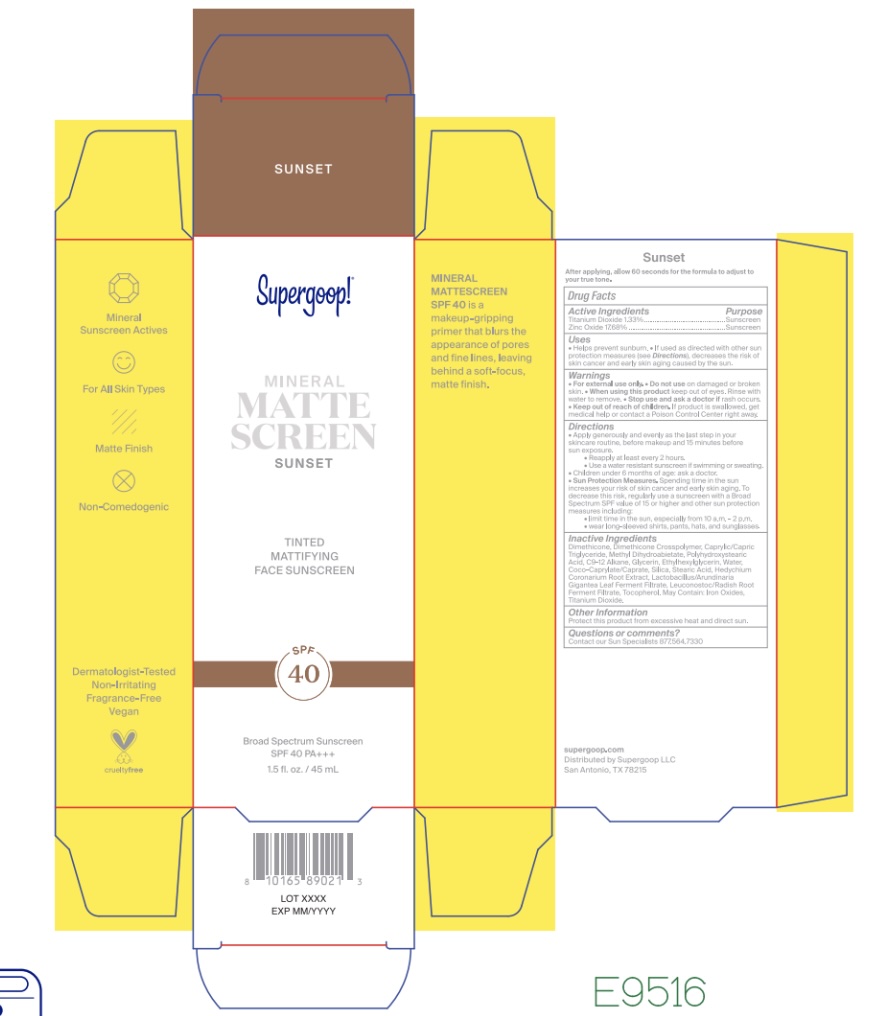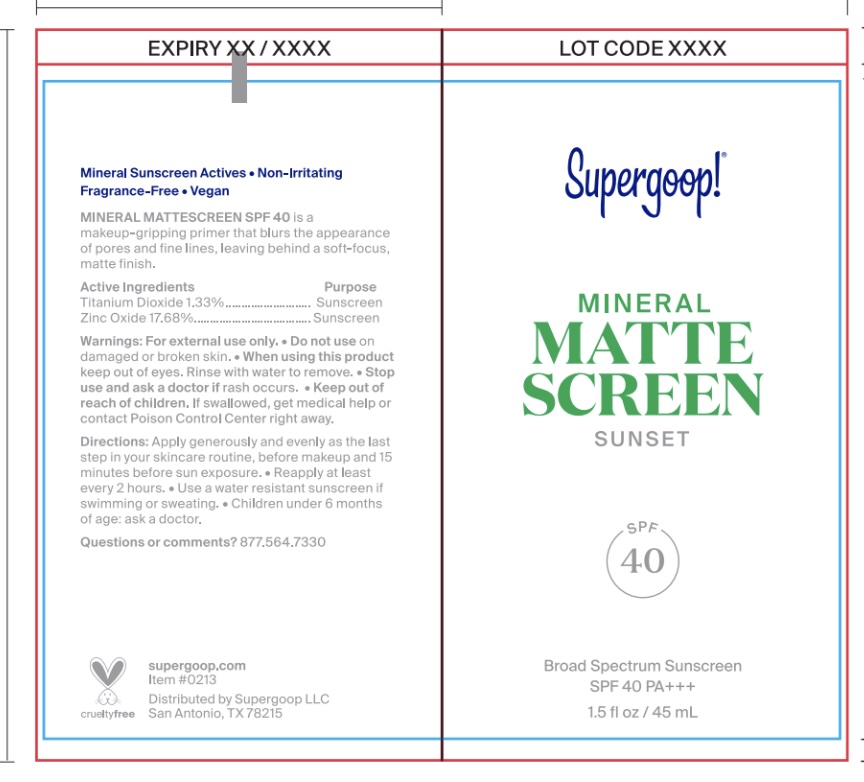 DRUG LABEL: Mineral Mattescreen SPF 40 - Sunset
NDC: 75936-664 | Form: LOTION
Manufacturer: Supergoop, LLC
Category: otc | Type: HUMAN OTC DRUG LABEL
Date: 20251118

ACTIVE INGREDIENTS: TITANIUM DIOXIDE 1.31 g/100 mL; ZINC OXIDE 17.68 g/100 mL
INACTIVE INGREDIENTS: GLYCERIN; SILICON DIOXIDE; METHYL DIHYDROABIETATE; POLYHYDROXYSTEARIC ACID (2300 MW); COCO-CAPRYLATE/CAPRATE; FERRIC OXIDE YELLOW; STEARIC ACID; FERRIC OXIDE RED; FERROSOFERRIC OXIDE; HEDYCHIUM CORONARIUM ROOT; LEUCONOSTOC/RADISH ROOT FERMENT FILTRATE; DIMETHICONE; DIMETHICONE CROSSPOLYMER (450000 MPA.S AT 12% IN CYCLOPENTASILOXANE); MEDIUM-CHAIN TRIGLYCERIDES; ETHYLHEXYLGLYCERIN; WATER; C9-12 ALKANE

Mineral Mattescreen SPF 40

Active Ingredients Purpose

Titanium Dioxide 1.31% Sunscreen

Zinc Oxide 17.68% Sunscreen

Uses

- Helps Prevent Sunburn
- If used as directed with other sun protection measures (see Directions), decreases the risk of skin cancer and early skin aging caused by the sun.

- Keep out of reach of children. If product is swallowed, get medical help or contact a poison Control Center right away

- Stop use and ask a doctor if rash occurs.

Warnings

- For external use only
- Do not use on damaged or broken skin.
- When using this product keep out of eyes. Rinse with water to remove.

Directions

- Apply generously and evenly 15 minutes before sun exposure
- Reapply at least every 2 hours.
- Use a water-resistant sunscreen if swimming or sweating
- Sun Protection Measures Spending time in the sun increases your risk of skin cancer and early skin aging. To decrease this risk, regularly use sunscreen with a Broad-Spectrum SPF value of 15 or higher and other sunprotection measures including: • limit your time in the sun, especially from 10a.m. – 2 p.m. • wear long-sleeved shirts, pants, hats, and sunglasses
- Children under 6 months of age: ask a doctor.

Inactive Ingredients

Dimethicone, Dimethicone Crosspolymer, Caprylic/Capric Triglyceride, Methyl Dihydroabietate, Polyhydroxystearic Acid, C9-12 Alkane, Glycerin, Ethylhexylglycerin, Water, Coco-Caprylate/Caprate, Silica, Stearic Acid, Hedychium Coronarium Root Extract, Lactobacillus/Arundinaria Gigantea Leaf Ferment Filtrate, Leuconostoc/Radish Root Ferment Filtrate, Tocopherol. May Contain: Iron Oxides, Titanium Dioxide

PACKAGE LABEL

Supergoop!

Mineral

MATTE
SCREEN

Sunrise/Sunset/Golden Hour

SPF 40

Broad Spectrum Sunscreen

SPF 40 PA +++

__ fl oz / __ mL

Golden Hour

Sunrise